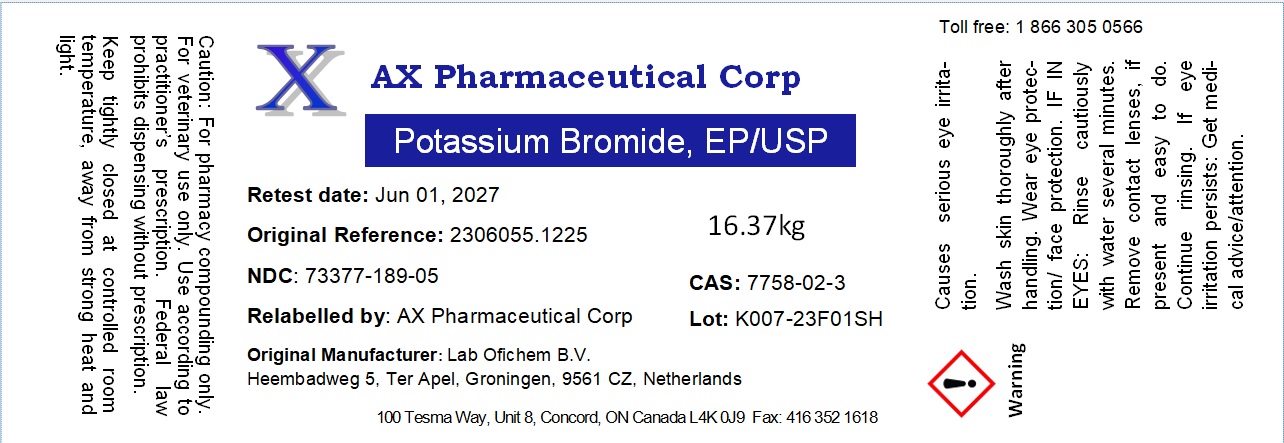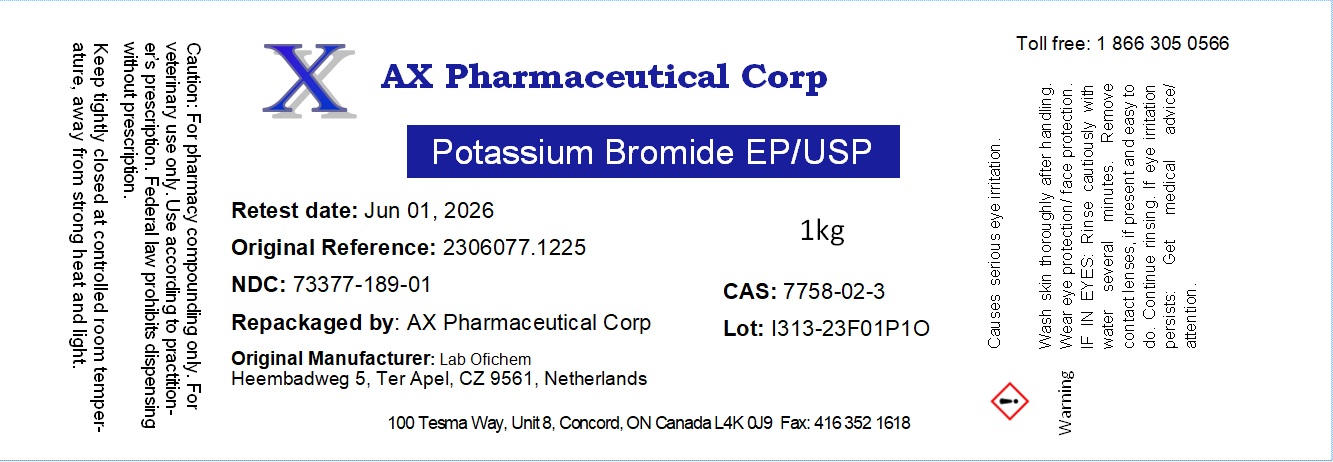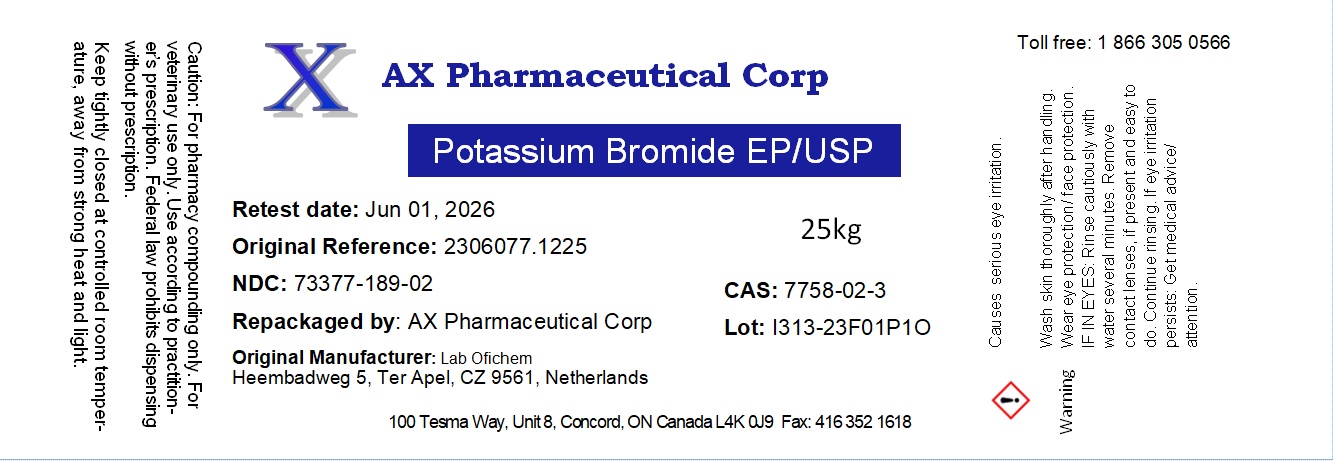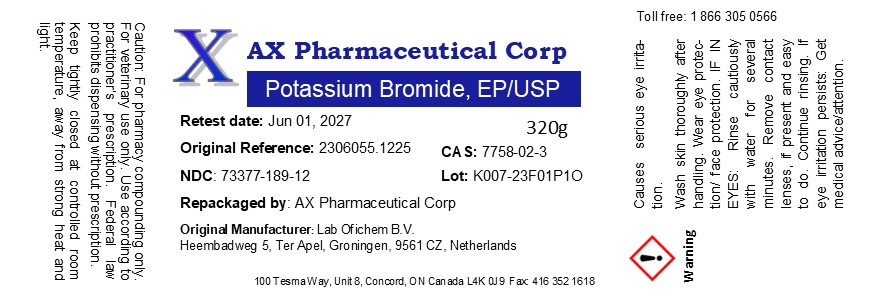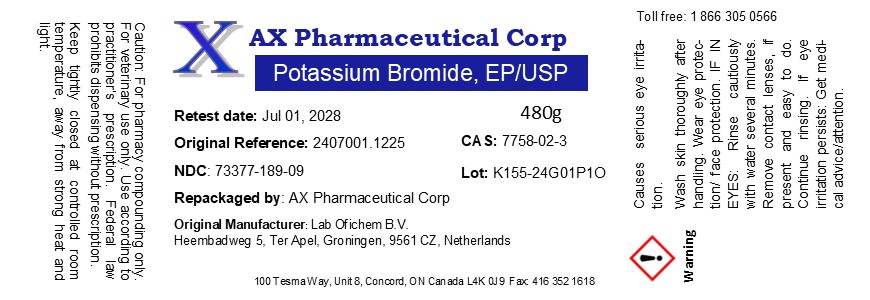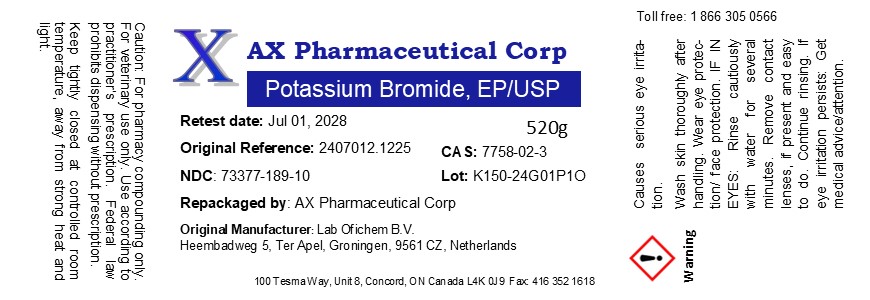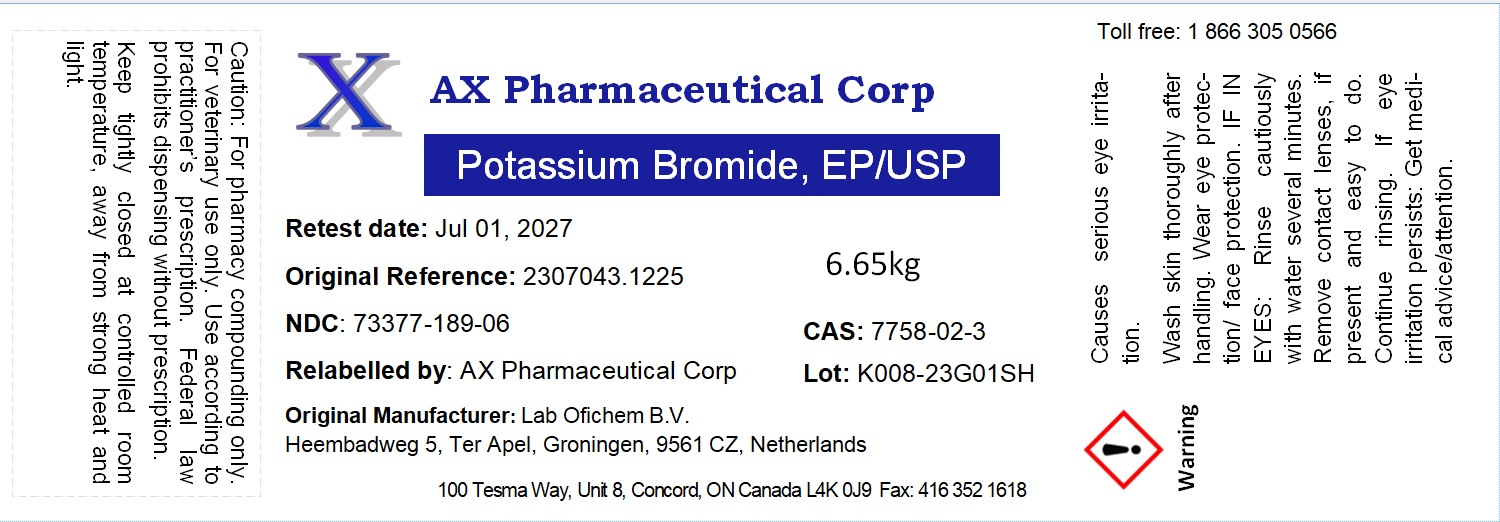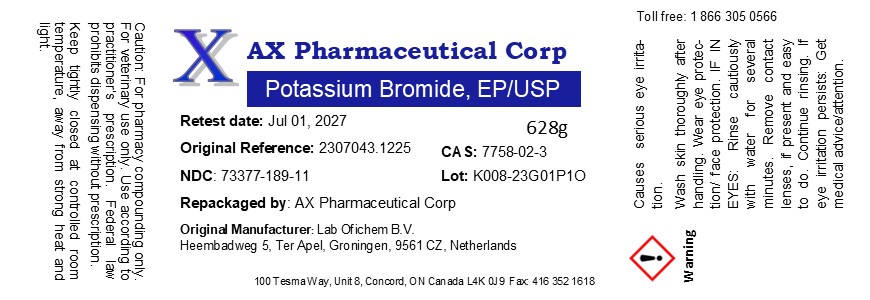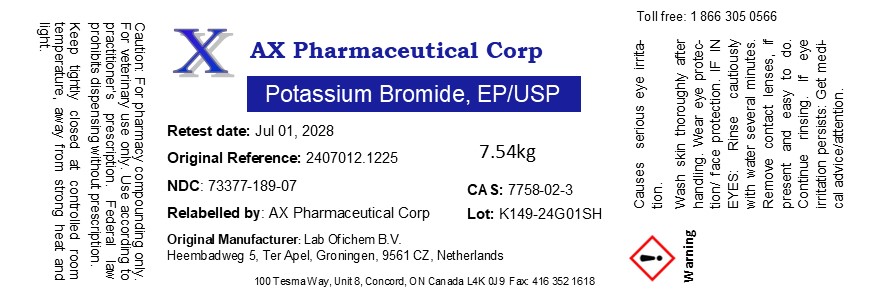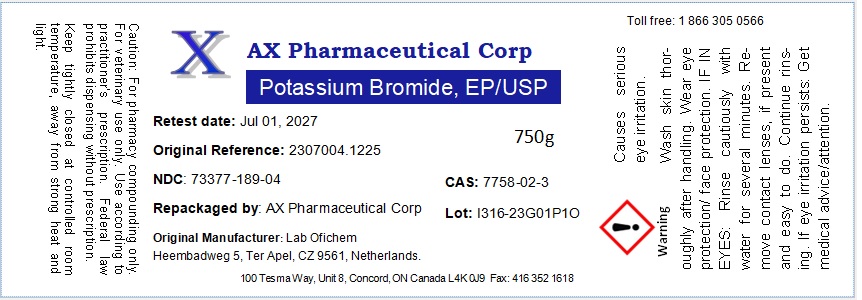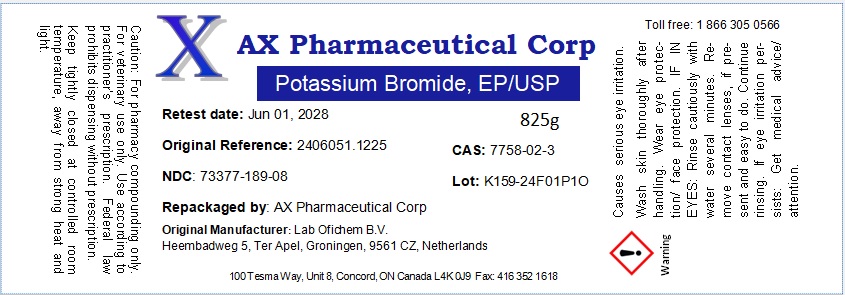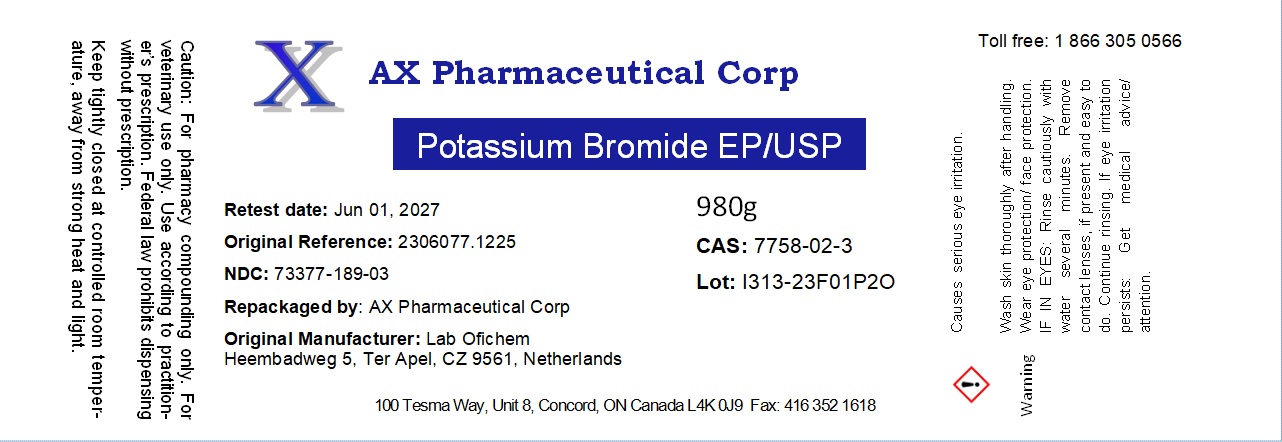 DRUG LABEL: Potassium Bromide
NDC: 73377-189 | Form: POWDER
Manufacturer: AX Pharmaceutical Corp
Category: other | Type: BULK INGREDIENT - ANIMAL DRUG
Date: 20251230

ACTIVE INGREDIENTS: POTASSIUM BROMIDE 1 g/1 g

Potassium Bromide